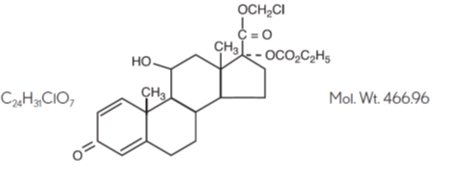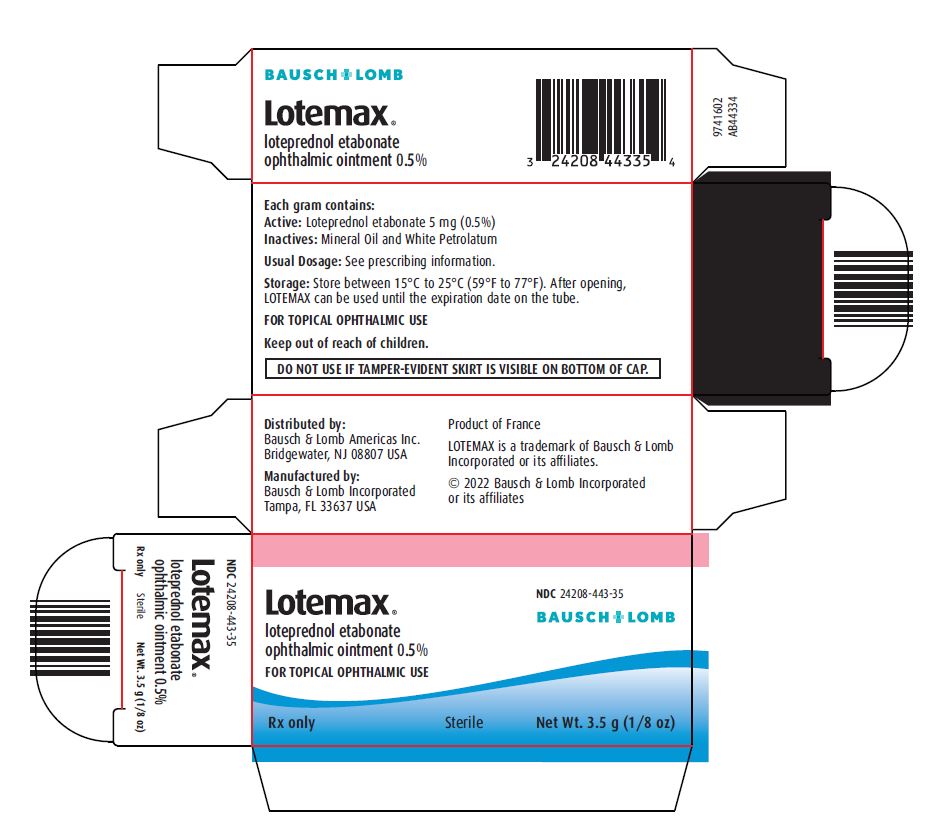 DRUG LABEL: Lotemax
NDC: 24208-443 | Form: OINTMENT
Manufacturer: Bausch & Lomb Incorporated
Category: prescription | Type: HUMAN PRESCRIPTION DRUG LABEL
Date: 20221130

ACTIVE INGREDIENTS: LOTEPREDNOL ETABONATE 5 mg/1 g
INACTIVE INGREDIENTS: MINERAL OIL; PETROLATUM

HIGHLIGHTS OF PRESCRIBING INFORMATION

These highlights do not include all the information needed to use LOTEMAX ointment safely and effectively. See full prescribing information for LOTEMAX ointment.
LOTEMAX® (loteprednol etabonate ophthalmic ointment) 0.5%, for topical ophthalmic use
Initial U.S. Approval: 1998

1 INDICATIONS AND USAGE

LOTEMAX ointment is a corticosteroid indicated for the treatment of post-operative inflammation and pain following ocular surgery. (1)

2 DOSAGE AND ADMINISTRATION

Apply a small amount (approximately ½ inch ribbon) into the conjunctival sac(s) four times daily beginning 24 hours after surgery and continuing throughout the first 2 weeks of the post-operative period. (2)

3 DOSAGE FORMS AND STRENGTHS

Ophthalmic ointment containing loteprednol etabonate 0.5%. (3)

4 CONTRAINDICATIONS

LOTEMAX ointment, as with other ophthalmic corticosteroids, is contraindicated in most viral diseases of the cornea and conjunctiva including epithelial herpes simplex keratitis (dendritic keratitis), vaccinia, and varicella, and also in mycobacterial infection of the eye and fungal diseases of ocular structures. (4)

5 WARNINGS AND PRECAUTIONS

- Intraocular Pressure (IOP) Increase: Prolonged use of corticosteroids may result in glaucoma with damage to the optic nerve, defects in visual acuity and fields of vision. If this product is used for 10 days or longer, IOP should be monitored even though it may be difficult in children and uncooperative patients. (5.1)
- Cataracts: Use of corticosteroids may result in posterior subcapsular cataract formation. (5.2)
- Delayed Healing: The use of steroids after cataract surgery may delay healing and increase the incidence of bleb formation. In those diseases causing thinning of the cornea or sclera, perforations have been known to occur with the use of topical steroids. (5.3)
- Bacterial Infections: Prolonged use of corticosteroids may suppress the host response and thus increase the hazard of secondary ocular infections. In acute purulent conditions, steroids may mask infection or enhance existing infection. (5.4)
- Viral Infections: Employment of a corticosteroid medication in the treatment of patients with a history of herpes simplex requires great caution. Use of ocular steroids may prolong the course and may exacerbate the severity of many viral infections of the eye (including herpes simplex). (5.5)
- Fungal Infections: Fungal infections of the cornea are particularly prone to develop coincidentally with long-term local steroid application. Fungus invasion must be considered in any persistent corneal ulceration where a steroid has been used or is in use. (5.6)

6 ADVERSE REACTIONS

The most common ocular adverse event, reported in approximately 25% of subjects in clinical studies, is anterior chamber inflammation. Other common adverse events, with an incidence of 4-5%, are conjunctival hyperemia, corneal edema, and eye pain. (6)

To report SUSPECTED ADVERSE REACTIONS, contact Bausch & Lomb Incorporated at 1‑800-553-5340 or FDA at 1-800-FDA-1088 or www.fda.gov/medwatch.

FULL PRESCRIBING INFORMATION

1 INDICATIONS AND USAGE

LOTEMAX® (loteprednol etabonate ophthalmic ointment) 0.5% ointment is a corticosteroid indicated for the treatment of post-operative inflammation and pain following ocular surgery.

2 DOSAGE AND ADMINISTRATION

Wash hands prior to using LOTEMAX ointment.

Apply a small amount (approximately ½ inch ribbon) into the conjunctival sac(s) four times daily beginning 24 hours after surgery and continuing throughout the first 2 weeks of the post-operative period.

3 DOSAGE FORMS AND STRENGTHS

Ophthalmic ointment containing loteprednol etabonate 0.5%.

4 CONTRAINDICATIONS

LOTEMAX ointment, as with other ophthalmic corticosteroids, is contraindicated in most viral diseases of the cornea and conjunctiva including epithelial herpes simplex keratitis (dendritic keratitis), vaccinia, and varicella, and also in mycobacterial infection of the eye and fungal diseases of ocular structures.

5 WARNINGS AND PRECAUTIONS

5.1 Intraocular Pressure (IOP) Increase

Prolonged use of corticosteroids may result in glaucoma with damage to the optic nerve, defects in visual acuity and fields of vision. Steroids should be used with caution in the presence of glaucoma. If this product is used for 10 days or longer, IOP should be monitored even though it may be difficult in children and uncooperative patients.

5.2 Cataracts

Use of corticosteroids may result in posterior subcapsular cataract formation.

5.3 Delayed Healing

The use of steroids after cataract surgery may delay healing and increase the incidence of bleb formation. In those diseases causing thinning of the cornea or sclera, perforations have been known to occur with the use of topical steroids.

The initial prescription and renewal of the medication order beyond 14 days should be made by a physician only after examination of the patient with the aid of magnification such as slit lamp biomicroscopy and, where appropriate, fluorescein staining.

5.4 Bacterial Infections

Prolonged use of corticosteroids may suppress the host response and thus increase the hazard of secondary ocular infections. In acute purulent conditions, steroids may mask infection or enhance existing infection. If signs and symptoms fail to improve after 2 days, the patient should be re-evaluated.

5.5 Viral Infections

Employment of a corticosteroid medication in the treatment of patients with a history of herpes simplex requires great caution. Use of ocular steroids may prolong the course and may exacerbate the severity of many viral infections of the eye (including herpes simplex).

5.6 Fungal Infections

Fungal infections of the cornea are particularly prone to develop coincidentally with long-term local steroid application. Fungus invasion must be considered in any persistent corneal ulceration where a steroid has been used or is in use. Fungal culture should be taken when appropriate.

5.7 Risk of Contamination

Do not touch the eyelid or surrounding areas with the tip of the tube. The cap should remain on the tube when not in use.

5.8 Contact Lens Wear

Patients should not wear contact lenses during their course of therapy with LOTEMAX ointment.

5.9 Topical Ophthalmic Use

LOTEMAX is not indicated for intraocular administration.

6 ADVERSE REACTIONS

Adverse reactions associated with ophthalmic steroids include elevated intraocular pressure, which may be associated with optic nerve damage, visual acuity and field defects, posterior subcapsular cataract formation, secondary ocular infection from pathogens including herpes simplex, and perforation of the globe where there is thinning of the cornea or sclera.

The most common ocular adverse event reported at approximately 25% in subjects in clinical studies with LOTEMAX ointment was anterior chamber inflammation. Other common adverse events, with an incidence of 4-5%, were conjunctival hyperemia, corneal edema, and eye pain. Many of these events may have been the consequence of the surgical procedure. The only non-ocular adverse event occurring at ≥ 1% was headache (1.5%).

8 USE IN SPECIFIC POPULATIONS

8.1 Pregnancy

Risk Summary

There are no adequate and well-controlled studies with loteprednol etabonate in pregnant women.

Loteprednol etabonate produced teratogenicity at clinically relevant doses in the rabbit and rat when administered orally during pregnancy. Loteprednol etabonate produced malformations when administered orally to pregnant rabbits at doses ≥ 1.6 times the recommended human ophthalmic dose (RHOD) and to pregnant rats at doses ≥ 41 times the RHOD. In pregnant rats receiving oral doses of loteprednol etabonate during the period equivalent to the last trimester of pregnancy through lactation in humans, survival of offspring was reduced at doses ≥ 4 times the RHOD. Maternal toxicity was observed in rats at doses ≥ 405 times the RHOD, and a maternal no observed adverse effect level (NOAEL) was established at 41 times the RHOD.

The background risk of major birth defects and miscarriage for the indicated population is unknown. However, the background risk in the U.S. general population of major birth defects is 2 to 4%, and of miscarriage is 15 to 20%, of clinically recognized pregnancies.

Data

Animal Data

Embryofetal studies were conducted in pregnant rabbits administered loteprednol etabonate by oral gavage on gestation Days 6 to 18, to target the period of organogenesis. Loteprednol etabonate produced fetal malformations at doses ≥ 0.1 mg/kg (1.6 times the recommended human ophthalmic dose (RHOD) based on body surface area, assuming 100% absorption). Spina bifida (including meningocele) was observed at doses ≥ 0.1 mg/kg, and exencephaly and craniofacial malformations were observed at doses ≥ 0.4 mg/kg (6.5 times the RHOD). At 3 mg/kg (49 times the RHOD), loteprednol etabonate was associated with increased incidences of abnormal left common carotid artery, limb flexures, umbilical hernia, scoliosis, and delayed ossification. Abortion and embryofetal lethality (resorption) occurred at doses ≥ 6 mg/kg (97 times the RHOD). A NOAEL for developmental toxicity was not established in this study. The NOAEL for maternal toxicity in rabbits was 3 mg/kg/day.

Embryofetal studies were conducted in pregnant rats administered loteprednol etabonate by oral gavage on gestation Days 6 to 15, to target the period of organogenesis. Loteprednol etabonate produced fetal malformations, including absent innominate artery at doses ≥ 5 mg/kg (41 times the RHOD); and cleft palate, agnathia, cardiovascular defects, umbilical hernia, decreased fetal body weight and decreased skeletal ossification at doses ≥ 50 mg/kg (410 times the RHOD). Embryofetal lethality (resorption) was observed at 100 mg/kg (811 times the RHOD). The NOAEL for developmental toxicity in rats was 0.5 mg/kg (4 times the RHOD). Loteprednol etabonate was maternally toxic (reduced body weight gain) at doses of ≥ 50 mg/kg/day. The NOAEL for maternal toxicity was 5 mg/kg.

A peri-/postnatal study was conducted in rats administered loteprednol etabonate by oral gavage from gestation Day 15 (start of fetal period) to postnatal Day 21 (the end of lactation period). At doses ≥ 0.5 mg/kg (4 times the clinical dose), reduced survival was observed in live-born offspring. Doses ≥ 5 mg/kg (41 times the RHOD) caused umbilical hernia/incomplete gastrointestinal tract. Doses ≥ 50 mg/kg (410 times the RHOD) produced maternal toxicity (reduced body weight gain, death), decreased number of live-born offspring, decreased birth weight, and delays in postnatal development. A developmental NOAEL was not established in this study. The NOAEL for maternal toxicity was 5 mg/kg.

8.2 Lactation

There are no data on the presence of loteprednol etabonate in human milk, the effects on the breastfed infant, or the effects on milk production. The developmental and health benefits of breastfeeding should be considered, along with the mother’s clinical need for LOTEMAX (loteprednol etabonate ophthalmic ointment) 0.5% and any potential adverse effects on the breastfed infant from LOTEMAX.

8.4 Pediatric Use

Safety and effectiveness in pediatric patients have not been established.

8.5 Geriatric Use

No overall differences in safety and effectiveness have been observed between elderly and younger adult patients.

11 DESCRIPTION

LOTEMAX® (loteprednol etabonate ophthalmic ointment) 0.5% is a sterile, topical corticosteroid for ophthalmic use. Loteprednol etabonate is a white to off-white powder.

Loteprednol etabonate is represented by the following structural formula:

Chemical name:

chloromethyl 17α-[(ethoxycarbonyl)oxy]-11β-hydroxy-3-oxoandrosta-1,4-diene-17β-carboxylate

Each gram contains:

Active: Loteprednol etabonate 5 mg (0.5%);

Inactives: Mineral Oil and White Petrolatum.

12 CLINICAL PHARMACOLOGY

12.1 Mechanism of Action

Corticosteroids inhibit the inflammatory response to a variety of inciting agents and probably delay or slow healing. They inhibit the edema, fibrin deposition, capillary dilation, leukocyte migration, capillary proliferation, fibroblast proliferation, deposition of collagen, and scar formation associated with inflammation. While glucocorticoids are known to bind to and activate the glucocorticoid receptor, the molecular mechanisms involved in glucocorticoid/glucocorticoid receptor‑dependent modulation of inflammation are not clearly established. However, corticosteroids are thought to inhibit prostaglandin production through several independent mechanisms.

12.3 Pharmacokinetics

The systemic exposure to loteprednol etabonate following ocular administration of LOTEMAX ointment has not been studied in humans. However, results from a bioavailability study with LOTEMAX suspension in normal volunteers established that plasma concentrations of loteprednol etabonate and Δ¹ cortienic acid etabonate (PJ 91), its primary, inactive metabolite, were below the limit of quantitation (1 ng/mL) at all sampling times. The results were obtained following the ocular administration of one drop in each eye of 0.5% loteprednol etabonate suspension, 8 times daily for 2 days or 4 times daily for 42 days. The maximum systemic exposure to loteprednol following administration of the ointment product dosed 4 times daily is not expected to exceed exposures attained with LOTEMAX suspension dosed up to two drops 4 times daily.

13 NONCLINICAL TOXICOLOGY

13.1 Carcinogenesis, Mutagenesis, Impairment of Fertility

Long-term animal studies have not been conducted to evaluate the carcinogenic potential of loteprednol etabonate. Loteprednol etabonate was not genotoxic in vitro in the Ames test, the mouse lymphoma tk assay, or in a chromosome aberration test in human lymphocytes, or in vivo in the single-dose mouse micronucleus assay.

Treatment of female and male rats with doses ≥ 25 mg/kg/day of loteprednol etabonate (203 times the RHOD based on body surface area, assuming 100% absorption) prior to and during mating caused preimplantation loss and decreased the number of live fetuses/live births. The NOAEL for fertility in rats was 5 mg/kg/day (41 times the RHOD).

14 CLINICAL STUDIES

In two independent, randomized, multicenter, double-masked, parallel-group, vehicle-controlled studies in 805 subjects meeting a protocol-specified threshold amount of anterior chamber inflammation, LOTEMAX ointment was more effective compared to its vehicle for complete resolution of post-operative anterior chamber cell, flare, and pain following cataract surgery. Primary endpoint was complete resolution of anterior chamber cells and flare (cell count of 0 and no flare) and no pain at post-operative Day 8. The individual clinical trial results are provided below.

In the two studies, LOTEMAX had statistically significant higher incidence of complete clearing of anterior chamber cells and flare at post-operative Day 8 (24-32% vs. 11-14%) and also had a statistically significant higher incidence of subjects that were pain free at post-operative Day 8 (73-78% vs. 41-45%).

16 HOW SUPPLIED/STORAGE AND HANDLING

LOTEMAX® (loteprednol etabonate ophthalmic ointment) 0.5% is a sterile ointment supplied in a tin tube with a pink polypropylene cap in the following size:

NDC 24208-443-35 3.5 g tube

DO NOT USE IF TAMPER-EVIDENT SKIRT IS VISIBLE ON BOTTOM OF CAP.

Storage: Store between 15°C to 25°C (59°F to 77°F). After opening, LOTEMAX can be used until the expiration date on the tube.

17 PATIENT COUNSELING INFORMATION

Risk of Contamination

Advise patients to wash hands prior to using LOTEMAX ointment.

Advise patients not to touch the eyelid or surrounding areas with the tip of the tube. The cap should remain on the tube when not in use.

Contact Lens Wear

Advise patients not to wear contact lenses during their course of therapy.

Risk of Secondary Infection

Advise patients to consult a physician if pain, redness, itching or inflammation becomes aggravated [see Warnings and Precautions (5.4)].

Distributed by:

Bausch & Lomb Americas Inc.

Bridgewater, NJ 08807 USA

Manufactured by:

Bausch & Lomb Incorporated

Tampa, FL 33637 USA

LOTEMAX is a trademark of Bausch & Lomb Incorporated or its affiliates.

© 2022 Bausch & Lomb Incorporated or its affiliates

9234905 (Folded)

9234805 (Flat)

PACKAGE/LABEL PRINCIPAL DISPLAY PANEL

NDC 24208-443-35

BAUSCH + LOMB

Lotemax®
loteprednol etabonate
ophthalmic ointment 0.5%

FOR TOPICAL OPHTHALMIC USE

Rx only

Sterile

Net. Wt. (3.5 g) 1/8oz.